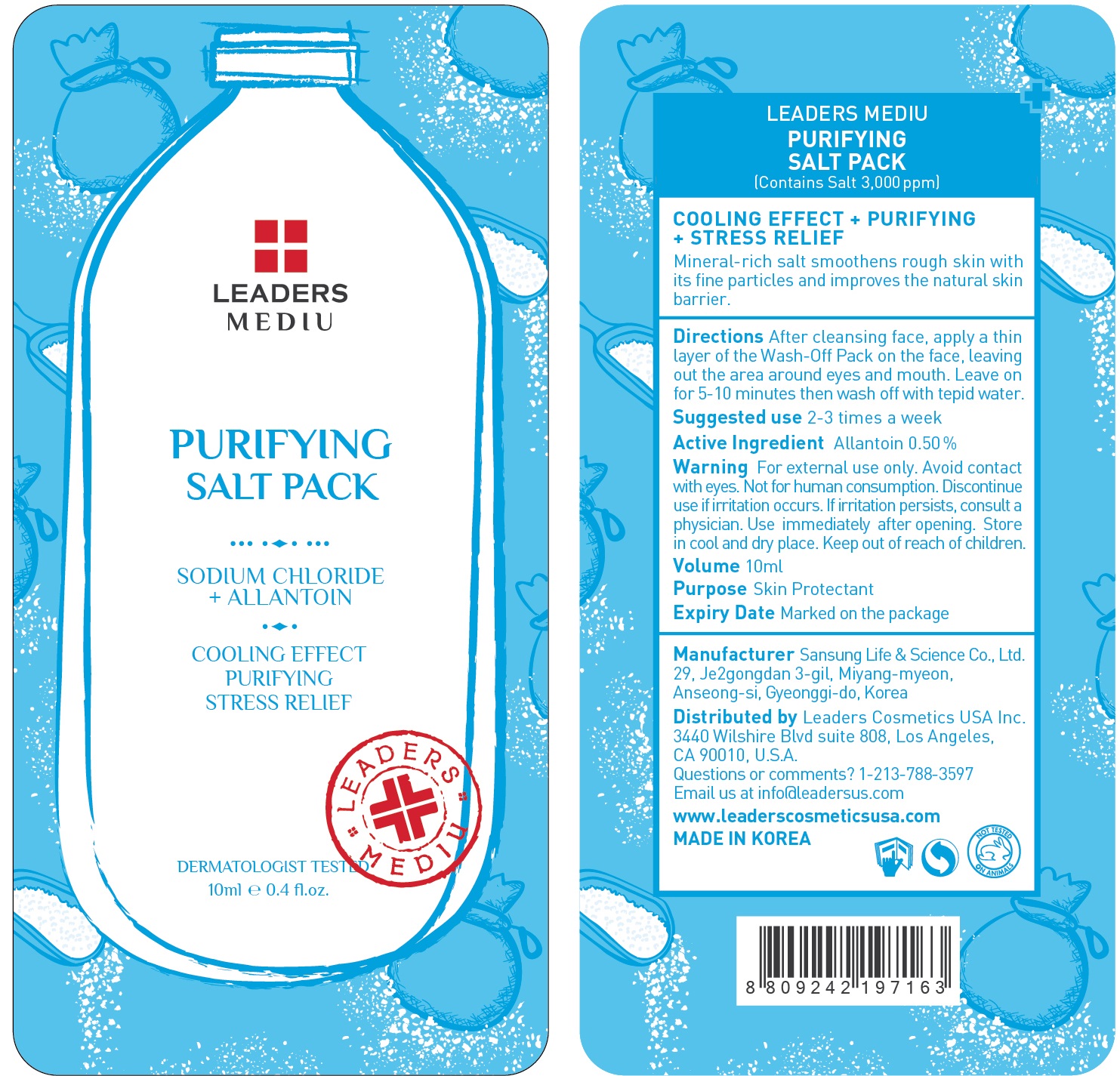 DRUG LABEL: Leaders Mediu Purifying Salt Pack
NDC: 69424-490 | Form: GEL
Manufacturer: SANSUNG LIFE & SCIENCE CO., LTD.
Category: otc | Type: HUMAN OTC DRUG LABEL
Date: 20160201

ACTIVE INGREDIENTS: Allantoin 50 mg/10 mL
INACTIVE INGREDIENTS: Water; Glycerin

ACTIVE INGREDIENT

Active Ingredient: Allantoin 0.50%

INACTIVE INGREDIENT

Inactive Ingredients: Water, Glycerin, Dipropylene Glycol, Butylene Glycol, Alcohol, Bentonite, Kaolin, Magnesium Aluminum Silicate, Polyvinyl Alcohol, Titanium Dioxide, Caprylic/Capric Triglyceride, Betaine, Sodium Chloride, Decylene Glycol, Ethylhexylglycerin, Hexylene Glycol, Boswellia serrata resin extract, Fragrance, Sodium Acrylate/Sodium Acryloyldimethyl Taurate Copolymer, Xanthan gum, Ferric Ammonium Ferrocyanide, Isohexadecane, Polysorbate 80, Rubus coreanus fruit extract, Cnidium officinale root extract, Snail secretion filtrate, Disodium EDTA, CI 19140, CI 42090, Totarol

PURPOSE

Purpose: Skin Protectant

WARNINGS

Warnings: For external use only. Avoid contact with eyes. Not for human consumption. Discontinue use if irritation occurs. If irritation persists, consult a physician.

Use immediately after opening. Store in cool and dry place. Keep out of reach of children.

KEEP OUT OF REACH OF CHILDREN

Directions

Directions: After cleansing face, apply a thin layer of the Wash-Off Pack on the face, leaving out the area around eyes and mouth. Leave on for 5-10 minutes then wash off with tepid water. *Suggested use is 2-3 times a week.

Directions

Directions: After cleansing face, apply a thin layer of the Wash-Off Pack on the face, leaving out the area around eyes and mouth. Leave on for 5-10 minutes then wash off with tepid water. *Suggested use is 2-3 times a week.